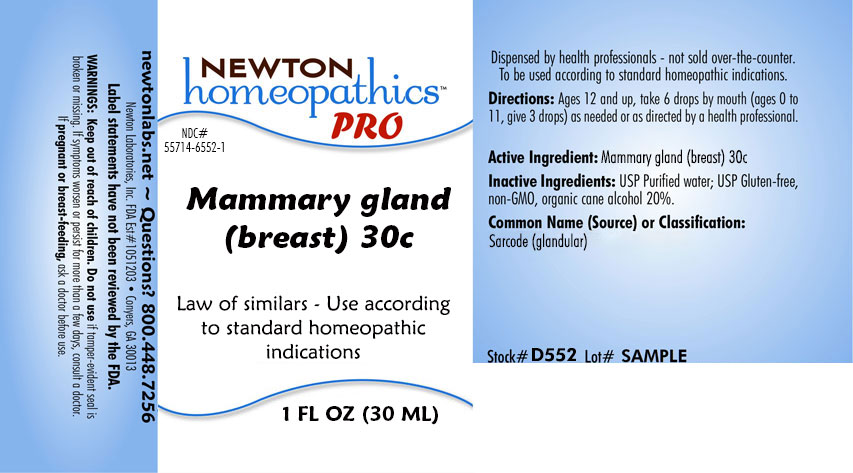 DRUG LABEL: Mammary Gland (Breast)
NDC: 55714-6552 | Form: LIQUID
Manufacturer: Newton Laboratories, Inc.
Category: homeopathic | Type: HUMAN OTC DRUG LABEL
Date: 20201216

ACTIVE INGREDIENTS: HUMAN MAMMARY GLAND 30 [hp_C]/1 mL
INACTIVE INGREDIENTS: ALCOHOL; WATER

Mammary 6552L

INDICATIONS & USAGE SECTION

Law of similars - Use according to standard homeopathic indications

DOSAGE & ADMINISTRATION SECTION

Directions: Ages 12 and up, take 6 drops by mouth (ages 0 to 11, give 3 drops) as needed or as directed by a health professional.

OTC - ACTIVE INGREDIENT SECTION

Mammary Gland (Breast) 30c

OTC - PURPOSE SECTION

Law of similars - Use according to standard homeopathic indications

INACTIVE INGREDIENT SECTION

Inactive Ingredients: USP Purified water; USP Gluten-free, non-GMO, organic cane alcohol 20%.

QUESTIONS SECTION

newtonlabs.net - Questions? 1.800.448.7256

Newton Laboratories, Inc. FDA Est # 1051203 - Conyers, GA 30013

WARNINGS SECTION

WARNINGS: Keep out of reach of children. Do not use if tamper-evident seal is broken or missing. If symptoms worsen or persist for more than a few days, consult a doctor. If pregnant or breast-feeding, ask a doctor before use.

OTC - PREGNANCY OR BREAST FEEDING SECTION

If pregnant or breast-feeding, ask a doctor before use.

OTC - KEEP OUT OF REACH OF CHILDREN SECTION

Keep out of reach of children.